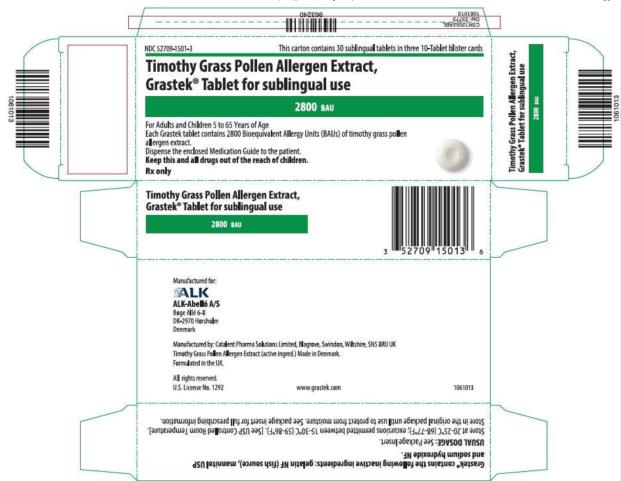 DRUG LABEL: GRASTEK
NDC: 52709-1501 | Form: TABLET
Manufacturer: ALK-Abello A S
Category: other | Type: STANDARDIZED ALLERGENIC
Date: 20220919

ACTIVE INGREDIENTS: PHLEUM PRATENSE POLLEN 2800 [BAU]/1 1
INACTIVE INGREDIENTS: MARINE COLLAGEN, SOLUBLE; MANNITOL; SODIUM HYDROXIDE

HIGHLIGHTS OF PRESCRIBING INFORMATION

These highlights do not include all the information needed to use GRASTEK safely and effectively. See full prescribing information for GRASTEK.
GRASTEK® (Timothy Grass Pollen Allergen Extract)
Tablet for Sublingual Use
Initial U.S. Approval: 2014

WARNING: SEVERE ALLERGIC REACTIONS

See full prescribing information for complete boxed warning.

• GRASTEK can cause life-threatening allergic reactions such as anaphylaxis and severe laryngopharyngeal restriction. (5.1)

• Do not administer GRASTEK to patients with severe, unstable or uncontrolled asthma. (4)

• Observe patients in the office for at least 30 minutes following the initial dose. (5.1)

• Prescribe auto-injectable epinephrine, instruct and train patients on its appropriate use, and instruct patients to seek immediate medical care upon its use. (5.2)

• GRASTEK may not be suitable for patients with certain underlying medical conditions that may reduce their ability to survive a serious allergic reaction. (5.2)

• GRASTEK may not be suitable for patients who may be unresponsive to epinephrine or inhaled bronchodilators, such as those taking beta-blockers. (5.2)

1 INDICATIONS AND USAGE

GRASTEK is an allergen extract indicated as immunotherapy for the treatment of grass pollen-induced allergic rhinitis with or without conjunctivitis confirmed by positive skin test or in vitro testing for pollen-specific IgE antibodies for Timothy grass or cross-reactive grass pollens. GRASTEK is approved for use in persons 5 through 65 years of age. (1)

2 DOSAGE AND ADMINISTRATION

For sublingual use only. (2)

- One tablet daily. (2.1)
- Initiate treatment at least 12 weeks before the expected onset of each grass pollen season and continue treatment throughout the season. For sustained effectiveness for one grass pollen season after cessation of treatment, GRASTEK may be taken daily for three consecutive years. (2.2)
- Place the tablet immediately under the tongue. Allow it to remain there until completely dissolved. Do not swallow for at least 1 minute. (2.2)
- Administer the first dose of GRASTEK under the supervision of a physician with experience in the diagnosis and treatment of allergic diseases. Observe patients in the office for at least 30 minutes following the initial dose. (2.2)

3 DOSAGE FORMS AND STRENGTHS

- Tablet, 2800 Bioequivalent Allergy Units (BAUs) (3)

4 CONTRAINDICATIONS

- Severe, unstable or uncontrolled asthma. (4)
- History of any severe systemic allergic reaction or any severe local reaction to sublingual allergen immunotherapy. (4)
- A history of eosinophilic esophagitis. (4)
- Hypersensitivity to any of the inactive ingredients contained in this product. (4)

5 WARNINGS AND PRECAUTIONS

- Inform patients of the signs and symptoms of serious allergic reactions and instruct them to seek immediate medical care and discontinue therapy should any of these occur. (5.1)
- In case of oral inflammation or wounds, stop treatment with GRASTEK to allow complete healing of the oral cavity. (5.7)

6 ADVERSE REACTIONS

- Adverse reactions reported in ≥5% of patients were: ear pruritus, oral pruritus, tongue pruritus, mouth edema, throat irritation. (6)

To report SUSPECTED ADVERSE REACTIONS, contact ALK-Abelló Inc, a subsidiary of ALK-Abelló A/S, at 1-855-216-6497 or FDA at 1-800-FDA-1088 or www.fda.gov/medwatch.

FULL PRESCRIBING INFORMATION

WARNING: SEVERE ALLERGIC REACTIONS

•GRASTEK can cause life-threatening allergic reactions such as anaphylaxis and severe laryngopharyngeal restriction. (5.1)

• Do not administer GRASTEK to patients with severe, unstable or uncontrolled asthma. (4)

• Observe patients in the office for at least 30 minutes following the initial dose. (5.1)

Prescribe auto-injectable epinephrine, instruct and train patients on its appropriate use, and instruct patients to seek immediate medical care upon its use. (5.2)

GRASTEK may not be suitable for patients with certain underlying medical conditions that may reduce their ability to survive a serious allergic reaction. (5.2)

GRASTEK may not be suitable for patients who may be unresponsive to epinephrine or inhaled bronchodilators, such as those taking beta-blockers. (5.2)

1 INDICATIONS AND USAGE

GRASTEK® is an allergen extract indicated as immunotherapy for the treatment of grass pollen-induced allergic rhinitis with or without conjunctivitis confirmed by positive skin test or in vitro testing for pollen-specific IgE antibodies for Timothy grass or cross-reactive grass pollens. GRASTEK is approved for use in persons 5 through 65 years of age.

GRASTEK is not indicated for the immediate relief of allergic symptoms.

2 DOSAGE AND ADMINISTRATION

For sublingual use only.

2.1 Dose

One GRASTEK tablet daily.

2.2 Administration

Administer the first dose of GRASTEK in a healthcare setting under the supervision of a physician with experience in the diagnosis and treatment of allergic diseases. After receiving the first dose of GRASTEK, observe the patient for at least 30 minutes to monitor for signs or symptoms of a severe systemic or a severe local allergic reaction. If the patient tolerates the first dose, the patient may take subsequent doses at home.

Administer GRASTEK to children under adult supervision.

Take the tablet from the blister unit after carefully removing the foil with dry hands.

Place the tablet immediately under the tongue. Allow it to remain there until completely dissolved. Do not swallow for at least 1 minute.

Wash hands after handling the tablet.

Do not take the tablet with food or beverage. Food or beverage should not be taken for the following 5 minutes after taking the tablet.

Initiate treatment at least 12 weeks before the expected onset of each grass pollen season and continue treatment throughout the season. For sustained effectiveness for one grass pollen season after cessation of treatment, GRASTEK may be taken daily for three consecutive years (including the intervals between the grass pollen seasons). The safety and efficacy of initiating treatment in season have not been established.

Data regarding the safety of restarting treatment after missing a dose of GRASTEK are limited. In the clinical trials, treatment interruptions for up to seven days were allowed.

Prescribe auto-injectable epinephrine to patients prescribed GRASTEK and instruct them in the proper use of emergency self-injection of epinephrine [see Warnings and Precautions (5.2)].

3 DOSAGE FORMS AND STRENGTHS

GRASTEK is available as 2800 Bioequivalent Allergy Unit (BAU) tablets that are white to off-white, circular with a debossed round detail on one side.

4 CONTRAINDICATIONS

GRASTEK is contraindicated in patients with:

- Severe, unstable or uncontrolled asthma
- A history of any severe systemic allergic reaction
- A history of any severe local reaction after taking any sublingual allergen immunotherapy
- A history of eosinophilic esophagitis
- Hypersensitivity to any of the inactive ingredients [gelatin, mannitol and sodium hydroxide] contained in this product [see Description (11)].

5 WARNINGS AND PRECAUTIONS

5.1 Severe Allergic Reactions

GRASTEK can cause systemic allergic reactions including anaphylaxis which may be life-threatening. In addition, GRASTEK can cause severe local reactions, including laryngopharyngeal swelling, which can compromise breathing and be life-threatening. Educate patients to recognize the signs and symptoms of these allergic reactions and instruct them to seek immediate medical care and discontinue therapy should any of these occur. Allergic reactions may require treatment with epinephrine. [See Warnings and Precautions (5.2).]

Administer the initial dose of GRASTEK in a healthcare setting under the supervision of a physician with experience in the diagnosis and treatment of allergic diseases and prepared to manage a life-threatening systemic or local allergic reaction. Observe patients in the office for at least 30 minutes following the initial dose of GRASTEK.

5.2 Epinephrine

Prescribe auto-injectable epinephrine to patients receiving GRASTEK. Instruct patients to recognize the signs and symptoms of a severe allergic reaction and in the proper use of emergency auto-injectable epinephrine. Instruct patients to seek immediate medical care upon use of auto-injectable epinephrine and to stop treatment with GRASTEK. [See Patient Counseling Information (17).]

See the epinephrine package insert for complete information.

GRASTEK may not be suitable for patients with certain medical conditions that may reduce the ability to survive a serious allergic reaction or increase the risk of adverse reactions after epinephrine administration. Examples of these medical conditions include but are not limited to: markedly compromised lung function (either chronic or acute), unstable angina, recent myocardial infarction, significant arrhythmia, and uncontrolled hypertension.

GRASTEK may not be suitable for patients who are taking medications that can potentiate or inhibit the effect of epinephrine. These medications include:

Βeta-adrenergic blockers: Patients taking beta-adrenergic blockers may be unresponsive to the usual doses of epinephrine used to treat serious systemic reactions, including anaphylaxis. Specifically, beta-adrenergic blockers antagonize the cardiostimulating and bronchodilating effects of epinephrine.

Alpha-adrenergic blockers, ergot alkaloids: Patients taking alpha-adrenergic blockers may be unresponsive to the usual doses of epinephrine used to treat serious systemic reactions, including anaphylaxis. Specifically, alpha-adrenergic blockers antagonize the vasoconstricting and hypertensive effects of epinephrine. Similarly, ergot alkaloids may reverse the pressor effects of epinephrine.

Tricyclic antidepressants, levothyroxine sodium, monoamine oxidase inhibitors and certain antihistamines: The adverse effects of epinephrine may be potentiated in patients taking tricyclic antidepressants, levothyroxine sodium, monoamine oxidase inhibitors, and the antihistamines chlorpheniramine, and diphenhydramine.

Cardiac glycosides, diuretics: Patients who receive epinephrine while taking cardiac glycosides or diuretics should be observed carefully for the development of cardiac arrhythmias.

5.3 Upper Airway Compromise

GRASTEK can cause local reactions in the mouth or throat that could compromise the upper airway [see Adverse Reactions (6.1 and 6.2)]. Consider discontinuation of GRASTEK in patients who experience persistent and escalating adverse reactions in the mouth or throat.

5.4 Eosinophilic Esophagitis

Eosinophilic esophagitis has been reported in association with sublingual tablet immunotherapy [see Contraindications (4) and Adverse Reactions (6.2)]. Discontinue GRASTEK and consider a diagnosis of eosinophilic esophagitis in patients who experience severe or persistent gastro-esophageal symptoms including dysphagia or chest pain.

5.5 Asthma

GRASTEK has not been studied in subjects with moderate or severe asthma or any subjects who required daily medication to treat asthma.

Withhold immunotherapy with GRASTEK if the patient is experiencing an acute asthma exacerbation. Reevaluate patients who have recurrent asthma exacerbations and consider discontinuation of GRASTEK.

5.6 Concomitant Allergen Immunotherapy

GRASTEK has not been studied in subjects who are receiving concomitant allergen immunotherapy. Concomitant dosing with other allergen immunotherapy may increase the likelihood of local or systemic adverse reactions to either subcutaneous or sublingual allergen immunotherapy.

5.7 Oral Inflammation

Stop treatment with GRASTEK to allow complete healing of the oral cavity in patients with oral inflammation (e.g., oral lichen planus, mouth ulcers or thrush) or oral wounds, such as those following oral surgery or dental extraction.

6 ADVERSE REACTIONS

Adverse reactions reported in ≥5% of patients were: ear pruritus, oral pruritus, tongue pruritus, mouth edema, and throat irritation.

6.1 Clinical Trials Experience

Because clinical trials are conducted under widely varying conditions, adverse reaction rates observed in the clinical trials of a drug cannot be directly compared to rates in the clinical trials of another drug and may not reflect the rates observed in clinical practice.

Adults

The safety data described below are based on 6 clinical trials which randomized 3589 subjects 18 through 65 years of age with Timothy grass pollen induced rhinitis with or without conjunctivitis, including 1669 subjects who were exposed to at least one dose of GRASTEK. Of the subjects treated with GRASTEK, 25% had mild asthma and 80% were sensitized to other allergens in addition to grass. The subject population was 88% White, 7% African American, and 3% Asian. Subjects were 52% male, and 88% of subjects were between 18 and 50 years of age. Subject demographics in placebo-treated subjects were similar to the active group.

The most common adverse reactions reported in subjects treated with GRASTEK were oral pruritus (26.7% vs 3.5% placebo), throat irritation (22.6% vs 2.8%), ear pruritus (12.5% vs 1.1%) and mouth edema (11.1% vs 0.8%). The percentage of subjects who discontinued from the clinical trials because of an adverse reaction while exposed to GRASTEK or placebo was 4.9% and 0.9%, respectively. The most common adverse reactions that led to study discontinuation in subjects who were exposed to GRASTEK were pharyngeal edema and oral pruritus.

Seven adult subjects (7/1669; 0.4%) who received GRASTEK experienced treatment-related systemic allergic reactions that led to discontinuation of GRASTEK in four out of the seven subjects.

- Five of the seven subjects had reactions on Day 1 of treatment with GRASTEK. Symptoms included swelling of lips/mouth; oral/pharyngeal itching; ear itching, sneezing, rhinorrhea, throat irritation, dysphonia, dysphagia, chest discomfort, and rash. Three of the five subjects received treatment with epinephrine and antihistamines, and one of the three also received oral corticosteroids. One of the five subjects who had a reaction on Day 1 of treatment with GRASTEK also had a reaction on Day 2 of treatment with GRASTEK. Symptoms on Day 2 included oral burning sensation; rhinorrhea; and throat irritation.
- One of the seven subjects had a reaction on Day 2 after tolerating treatment with GRASTEK on Day 1. Symptoms included edema of the lower lip, epigastric discomfort and dizziness.
- One of the seven subjects developed chest tightness and shortness of breath on Day 42 of treatment with GRASTEK.

Adverse reactions reported in ≥1% of subjects treated with GRASTEK are shown in Table 1.

Table 1: Adverse Reactions Reported in ≥1% of Adults Treated with GRASTEK

Adverse Reaction | GRASTEK (N=1669) | PLACEBO (N=1645)
Nervous System Disorders Headache | 2.1% | 1.3%
Ear and Labyrinth Disorders Ear pruritus | 12.5% | 1.1%
Respiratory, Thoracic and Mediastinal Disorders Throat irritation Pharyngeal edema Dry throat Oropharyngeal pain Nasal discomfort Throat tightness Dyspnea | 22.6% 3.4% 1.7% 1.6% 1.6% 1.4% 1.1% | 2.8% 0.1% 0.4% 1.0% 1.0% 0.2% 0.4%
Gastrointestinal Disorders Oral pruritus Mouth edema Paresthesia oral Tongue pruritus Lip swelling Swollen tongue Dyspepsia Hypoesthesia oral Nausea Oral discomfort Oral mucosal erythema Lip edema Glossitis Stomatitis Tongue disorder Tongue edema Glossodynia Dysphagia Palatal edema | 26.7% 11.1% 9.8% 5.7% 4.0% 2.8% 2.3% 2.3% 1.9% 1.6% 1.5% 1.3% 1.3% 1.1% 1.1% 1.1% 1.0% 1.0% 1.0% | 3.5% 0.8% 2.0% 0.5% 0.2% 0.1% 0.1% 1.0% 0.6% 0.3% 0.6% 0.1% 0.1% 0.3% 0.2% 0.4% 0.3% 0.2% 0.1%
Skin and Subcutaneous Tissue Disorders Pruritus Urticaria | 2.4% 1.7% | 1.0% 0.9%
General Disorders and Administration Site Conditions Chest discomfort Fatigue | 1.6% 1.4% | 0.5% 0.4%

Adverse reactions of interest that occurred in ≤1% of GRASTEK recipients include abdominal pain and gastroesophageal reflux.

Pediatrics

Safety data are based on 3 clinical trials which randomized 881 subjects between 5 and 17 years of age with grass pollen induced rhinitis with or without conjunctivitis. Overall, 445 subjects received at least one dose of GRASTEK. Of the subjects treated with GRASTEK, 31% had mild asthma and 86% were sensitized to other allergens in addition to grass. The subject population was 86% White, 7% African American and 3% multi-racial. The majority (66%) of subjects were male. The mean age of subjects was 11.7 years. Subject demographics in placebo-treated subjects were similar to the active group.

The most common adverse reactions in pediatric subjects treated with GRASTEK were oral pruritus (24.4% vs 2.1% placebo), throat irritation (21.3% vs 2.5%) and mouth edema (9.8% vs 0.2%). The percentage of subjects who discontinued from the clinical trials because of an adverse reaction while exposed to GRASTEK or placebo was 6.3% and 0.7%, respectively.

One pediatric subject (1/447; 0.2%) who received GRASTEK experienced a treatment-related systemic allergic reaction consisting of lip angioedema, slight dysphagia due to the sensation of a lump in the throat, and intermittent cough which was of moderate intensity on Day 1. The subject was treated with epinephrine, recovered, and was discontinued from the trial.

Adverse reactions reported in ≥1% of subjects treated with GRASTEK are shown in Table 2.

Table 2: Adverse Reactions Reported in ≥1% of Pediatric Subjects Treated with GRASTEK

Adverse Reaction | GRASTEK (N=447) | PLACEBO (N=434)
Nervous System Disorders Headache | 3.4% | 1.8%
Ear and Labyrinth Disorders Ear pruritus | 7.2% | 0.5%
Eye Disorders Eye pruritus | 3.4% | 2.1%
Respiratory, Thoracic and Mediastinal Disorders Throat irritation Oropharyngeal pain Pharyngeal erythema Pharyngeal edema Cough Dyspnea Nasal discomfort Nasal congestion Sneezing | 21.3% 4.0% 3.6% 2.9% 2.7% 2.0% 1.6% 1.6% 1.6% | 2.5% 1.4% 0.7% 0% 1.2% 0.5% 0.9% 0.5% 0.7%
Gastrointestinal Disorders Oral pruritus Mouth edema Tongue pruritus Lip swelling Paresthesia oral Oral mucosal erythema Lip pruritus Swollen tongue Dysphagia Nausea Oral discomfort Stomatitis Hypoesthesia oral Glossodynia | 24.4% 9.8% 9.2% 7.2% 5.4% 4.9% 2.9% 2.5% 2.0% 1.6% 1.6% 1.3% 1.1% 1.1% | 2.1% 0.2% 0.9% 0.5% 1.2% 0.9% 0.2% 0% 0% 0.5% 0.2% 0% 0.2% 0.2%
Skin and Subcutaneous Tissue Disorders Urticaria | 1.8% | 0.2%
General Disorders and Administration Site Conditions Chest discomfort | 2.0% | 0.5%

6.2 Postmarketing Experience

Postmarketing Safety Studies

In European post-approval studies which included 1,666 patients treated with GRASTEK (marketed under the name GRAZAX), reported serious adverse reactions assessed as related to GRASTEK use included anaphylactic reaction, asthma exacerbation, hoarseness, laryngitis, oral ulceration, and ulcerative colitis exacerbation.

Spontaneous Postmarketing Reports

The following adverse reactions have been identified during post-approval use of GRASTEK (marketed under the name GRAZAX in Europe). Because these reactions are reported voluntarily from a population of uncertain size, it is not always possible to reliably estimate their frequency or establish a causal relationship to drug exposure. These include:

- Ear and Labyrinth Disorders: ear discomfort, ear swelling
- Eye Disorders: eye swelling
- Gastrointestinal Disorders: cheilitis, diarrhea, dry mouth, enlarged uvula, eosinophilic esophagitis, gastritis, lip blister, oral pain, salivary hypersecretion, vomiting
- General disorder and administration site conditions: chest pressure, face edema, sensation of foreign body, swelling of neck
- Immune System Disorders: serious systemic allergic reactions, including anaphylaxis, anaphylactic shock
- Infections and Infestations: pneumonia
- Investigations: heart rate increased, heart rate irregular, oxygen saturation decreased, peak expiratory flow rate decreased
- Nervous System Disorders: altered state of consciousness, dizziness, drowsiness, dysgeusia, paresthesia, tremor, difficulty speaking, paresthesia (including hypoesthesia and burning sensation in extremities)
- Respiratory, Thoracic and Mediastinal Disorders: asthma exercise induced, bronchospasm, hyperventilation, laryngeal discomfort, respiratory distress, status asthmaticus, stridor, throat pruritus, wheezing
- Skin and Subcutaneous Tissue Disorders: angioedema, erythema, erythema facial, rash
- Vascular Disorders: hypotension.

Eosinophilic esophagitis has been reported following treatment with GRASTEK (marketed under the name GRAZAX). The clinical details of some postmarketing reports are consistent with a drug-induced effect, including at least one case with resolution of symptoms upon discontinuation of GRASTEK, relapse after resuming GRASTEK and resolution again after discontinuation of GRASTEK.

8 USE IN SPECIFIC POPULATIONS

8.1 Pregnancy

Risk Summary

All pregnancies have a risk of birth defect, loss, or other adverse outcomes. In the U.S. general population, the estimated background risk of major birth defects and miscarriage in clinically recognized pregnancies is 2 to 4% and 15 to 20%, respectively. Available human data do not establish the presence or absence of GRASTEK-associated risks during pregnancy.

In two reproductive and developmental toxicity studies mice were administered Timothy grass pollen extract daily by buccal cavity at doses approximately 6.7 times the human sublingual dose. In one study doses were administered during gestation and lactation. In the other study doses were administered prior to mating and during gestation. These studies revealed no evidence of harm to the mother or the fetus due to GRASTEK (see 8.1 Data).

Data

Animal Data

A pre- and postnatal developmental study and a combined fertility/developmental toxicity study were conducted in mice. In these studies, the effect of Timothy grass (Phleum pratense) pollen allergen extract, the active component of GRASTEK, on embryo-fetal development was evaluated. In the pre- and postnatal developmental toxicity study female mice were administered Timothy grass pollen allergen extract by buccal cavity daily from day 6 of gestation to day 17 of lactation at doses approximately 6.7 times the human sublingual dose. In the combined fertility/developmental toxicity study, female mice were administered Timothy grass pollen allergen extract daily by buccal cavity administration from 14 days prior to mating and until day 15 of the gestation period (male animals were administered the same dose daily for 4 weeks before pairing and during pairing) at doses approximately 6.7 times the human sublingual dose. Fertility was normal and there were no treatment-related post-implementation losses, fetal malformations or variations.

8.2 Lactation

Risk Summary

It is not known if GRASTEK is excreted in human milk. Data are not available to assess the effect of GRASTEK on milk production or on the breast-fed child. The developmental and health benefits of breastfeeding should be considered along with the mother’s clinical need for GRASTEK and any potential adverse effects on the breast-fed child from GRASTEK or from the underlying maternal condition.

8.4 Pediatric Use

Efficacy and safety of GRASTEK have been established in children and adolescents 5 through 17 years of age. The safety and efficacy in pediatric patients below 5 years of age have not been established.

8.5 Geriatric Use

There is no clinical trial experience with GRASTEK in patients over 65 years of age.

11 DESCRIPTION

GRASTEK tablets contain pollen allergen extract from Timothy grass (Phleum pratense). GRASTEK is a sublingual tablet.

GRASTEK is available as a tablet of 2800 BAU of Timothy grass pollen allergen extract.

Inactive ingredients: gelatin NF (fish source), mannitol USP and sodium hydroxide NF.

12 CLINICAL PHARMACOLOGY

12.1 Mechanism of Action

The precise mechanisms of action of allergen immunotherapy are not known.

13 NONCLINICAL TOXICOLOGY

13.1 Carcinogenesis, Mutagenesis, Impairment of Fertility

No studies have been performed in animals to evaluate the carcinogenic potential of GRASTEK.

There were no positive findings in the in vitro mouse lymphoma and the bacterial reverse mutation assays for mutagenicity using Timothy grass (Phleum pratense) pollen allergen extract.

A combined fertility/developmental toxicity study in male and female mice revealed no evidence of impaired fertility due to Timothy grass pollen allergen extract administered daily prior to mating and during gestation at approximately 6.7 times the human sublingual dose (see 8.1 Data).

14 CLINICAL STUDIES

The efficacy of GRASTEK in the treatment of allergic rhinitis with or without conjunctivitis in Timothy grass pollen allergic subjects 5 years of age and older, with or without mild asthma, was evaluated during the first grass pollen season in two trials of approximately 24 weeks treatment duration. The sustained effect of GRASTEK was evaluated in one trial conducted over 5 grass pollen seasons. All three trials were randomized, double-blind, parallel group, multicenter clinical trials. Subjects had a history of grass pollen induced rhinitis with or without conjunctivitis and sensitivity to Timothy grass pollen as determined by specific testing (IgE). In these three studies, subjects initiated GRASTEK or placebo approximately 12 weeks prior to the pollen season. In the long-term study, subjects received GRASTEK or placebo daily for 3 consecutive years and were followed for 2 years without treatment.

Efficacy was established by self-reporting of rhinoconjunctivitis daily symptom scores (DSS) and daily medication scores (DMS). Daily rhinoconjunctivitis symptoms included four nasal symptoms (runny nose, stuffy nose, sneezing, and itchy nose), and two ocular symptoms (gritty/itchy eyes and watery eyes). The rhinoconjunctivitis symptoms were measured on a scale of 0 (none) to 3 (severe). Subjects in clinical trials were allowed to take symptom-relieving medications (including systemic and topical antihistamines and topical and oral corticosteroids) as needed. The daily medication score measured the use of standard open-label allergy medications. Predefined values were assigned to each class of medication. Generally, systemic and topical antihistamines were given the lowest score, topical steroids an intermediate score, and oral corticosteroids the highest score. The sums of the DSS and DMS were combined into the Total Combined Score (TCS) which was averaged over the entire grass pollen season.

14.1 First Season Efficacy

Adults and Children

This placebo-controlled trial evaluated 1501 subjects 5 through 65 years of age (approximately 80% were 18 years and older) comparing GRASTEK (N=752) and placebo (N=749) administered as a sublingual tablet daily for approximately 24 weeks. The subject population was 84% White, 9% African American and 4% Asian. The majority of subjects were male (52%). In this study, approximately 25% of subjects had mild, intermittent asthma and 85% of all subjects were sensitized to other allergens in addition to grass pollen. Subjects with a clinical history of symptomatic allergies to non-grass pollen allergens that required treatment during the grass pollen season were excluded from the studies. All treatment groups were balanced with regard to baseline characteristics.

Subjects treated with GRASTEK had a decrease in the TCS throughout the grass pollen season compared to placebo-treated subjects. Similarly, the DSS and DMS were decreased in subjects treated with GRASTEK compared to placebo throughout the grass pollen season, and the TCS was decreased compared to placebo during the peak grass pollen season (see Table 3).

Table 3: Total Combined Scores (TCS), Rhinoconjunctivitis Daily Symptom Scores (DSS), and Daily Medication Scores (DMS) During the Grass Pollen Season

Endpoint* | GRASTEK (N)† Score‡ | Placebo (N)† Score‡ | Treatment Difference (GRASTEK – Placebo) | Difference Relative to Placebo§ Estimate (95% CI)
TCS Entire Season | (629) 3.24 | (672) 4.22 | -0.98 | -23% (-36.0, -13.0)
TCS Peak Season | (620) 3.33 | (663) 4.67 | -1.33 | -29% (-39.0, -15.0)
DSS Entire Season | (629) 2.49 | (672) 3.13 | -0.64 | -20% (-32.0, -10.0)
DMS Entire Season | (629) 0.88 | (672) 1.36 | -0.48 | -35% (-49.3, -20.8)

TCS=Total Combined Score (DSS + DMS); DSS=Daily Symptom Score; DMS=Daily Medication Score.

* Non-parametric analysis for TCS and DSS endpoints: Parametric analysis using zero-inflated log-normal model for DMS.

† Number of subjects in analyses.

‡ For TCS and DSS endpoints the group medians are reported, treatment difference and that relative to placebo is based on group medians. For DMS, the group means are reported and difference relative to placebo is based on estimated group means.

§ Difference relative to placebo computed as: (GRASTEK - placebo)/placebo x 100.

Children

This double-blind clinical trial of approximately 24 weeks duration evaluated 344 pediatric subjects 5 to 17 years of age who were treated with either GRASTEK or placebo once daily. The subject population was 88% White, 7% African American, and 2% Asian. The majority (65%) of subjects were male. The mean age of subjects was 12.3 years. In this study, 26% of subjects had mild intermittent asthma and most subjects (89%) were sensitized to other allergens in addition to grass pollen. Subjects with a clinical history of symptomatic allergies to non-grass pollen allergens that required treatment during the grass pollen season were excluded from the studies. All treatment groups were balanced with regard to baseline characteristics.

Pediatric subjects treated with GRASTEK had a decrease in TCS throughout the grass pollen season compared to placebo treated subjects (see Table 4). Similarly, the DSS and DMS were decreased in GRASTEK compared to placebo throughout the grass pollen season.

Table 4: Total Combined Scores (TCS), Rhinoconjunctivitis Daily Symptom Scores (DSS) and Daily Medication Scores (DMS) During the Entire Grass Pollen Season

Endpoint* | GRASTEK (N=149)† Score‡ | Placebo (N=158)† Score‡ | Treatment Difference (GRASTEK – Placebo) | Difference Relative to Placebo§ Estimate (95% CI)
TCS | 4.62 | 6.25 | -1.63 | -26% (-38.2, -10.1)
DSS | 3.71 | 4.91 | -1.20 | -24% (-36.4, -9.1)
DMS | 0.91 | 1.33 | -0.42 | -32% (-57.7, 4.0)

TCS=Total combined score (DSS + DMS); DSS=Daily Symptom Score; DMS=Daily Medication Score.

* Parametric analysis using analysis of variance model for all endpoints.

† Number of subjects in analyses.

‡ The estimated group means are reported and difference relative to placebo is based on estimated group means.

§ Difference relative to placebo computed as: (GRASTEK - placebo)/placebo x 100.

14.2 Sustained Effect

Adult Subjects 18 Years and Older

The sustained effect of GRASTEK was measured in a 5-year double-blind study. The study included 634 randomized subjects between 18 and 65 years of age. The subject population was 96% White, 2% Asian and 1% African American. The majority (59%) of subjects were male. The mean age of subjects was 34 years. Subjects received either GRASTEK or placebo daily for 3 consecutive years and were then observed for 2 subsequent years during which they did not receive study drug. Subjects treated with GRASTEK had a decrease in TCS throughout the grass pollen season during the three years of active treatment. This effect was sustained during the grass pollen season in the first year after discontinuation of GRASTEK (see Table 5), but not in the second year.

Table 5: Rhinoconjunctivitis Total Combined Score (TCS), Daily Symptom Score (DSS), and Daily Medication Score (DMS) During the Entire Grass Pollen Season from the 5-Year Study

Endpoint | Difference Relative to Placebo* (95% CI)
 | Treatment Year 1 N=568† | Treatment Year 2‡ N=316† | Treatment Year 3 N=287† | Post Treatment Year 1 N=257†
TCS | -34.2% (-42.0%, -26.3%) | -40.9% (-51.8%, -29.5%) | -34.0% (-45.5%, -21.4%) | -27.2% (-39.9%, -12.4%)
DSS | -31.2% (-38.8%, -23.4%) | -36.2% (-46.5%, -26.2%) | -29.0% (-40.3%, -16.3%) | -26.2% (-37.6%, -12.2%)
DMS | -38.4% (-49.8%, -26.5%) | -45.5% (-60.4%, -28.2%) | -40.1% (-55.4%, -21.2%) | -28.6% (-46.3%, -6.0%)

TCS=Total Combined Score (DSS + DMS); DSS=Daily Symptom Score; DMS=Daily Medication Score.

* Difference relative to placebo computed as: (GRASTEK - placebo)/placebo x 100.

† Number of subjects in analyses.

‡ Study extended from 1 to 5 years (site closures, subject unwillingness to participate beyond 1 year).

16 HOW SUPPLIED/STORAGE AND HANDLING

GRASTEK 2800 BAU tablets are white to off-white, circular sublingual tablets with a debossed round detail on one side.

GRASTEK is supplied as follows:

3 blister packages of 10 tablets (30 tablets total). NDC 52709-1501-3

Store at controlled room temperature 20ºC-25ºC (68ºF-77ºF); excursions permitted between 15ºC-30ºC (59ºF-86ºF). Store in the original package until use to protect from moisture.

17 PATIENT COUNSELING INFORMATION

Advise patients to read the FDA-approved patient labeling (Medication Guide) and to keep GRASTEK and all medicines out of the reach of children.

Severe Allergic Reactions

Advise patients that GRASTEK may cause life-threatening systemic or local allergic reactions, including anaphylaxis. Educate patients about the signs and symptoms of these allergic reactions [see Warnings and Precautions (5.1)]. The signs and symptoms of a severe allergic reaction may include: syncope, dizziness, hypotension, tachycardia, dyspnea, wheezing, bronchospasm, chest discomfort, cough, abdominal pain, vomiting, diarrhea, rash, pruritus, flushing, and urticaria.

Ensure that patients have auto-injectable epinephrine and instruct patients in its proper use. Instruct patients who experience a severe allergic reaction to seek immediate medical care, discontinue GRASTEK, and resume treatment only when advised by a physician to do so. [See Warnings and Precautions (5.2).]

Advise patients to read the patient information for epinephrine.

Inform patients that the first dose of GRASTEK must be administered in a healthcare setting under the supervision of a physician and that they will be monitored for at least 30 minutes to watch for signs and symptoms of a life-threatening systemic or local allergic reaction [see Warnings and Precautions (5.1)].

Because of the risk of upper airway compromise, instruct patients with persistent and escalating adverse reactions in the mouth or throat to discontinue GRASTEK and to contact their healthcare professional. [See Warnings and Precautions (5.3).]

Because of the risk of eosinophilic esophagitis, instruct patients with severe or persistent symptoms of esophagitis to discontinue GRASTEK and to contact their healthcare professional. [See Warnings and Precautions (5.4).]

Inform parents/guardians that GRASTEK should only be administered to children under adult supervision [see Dosage and Administration (2.2)].

Asthma

Instruct patients with asthma that if they have difficulty breathing or if their asthma becomes difficult to control, they should stop taking GRASTEK and contact their healthcare professional immediately [see Warnings and Precautions (5.5)].

Administration Instructions

Instruct patients to carefully remove the foil from the blister unit with dry hands and then take the sublingual tablet immediately by placing it under the tongue where it will dissolve. Also instruct patients to wash their hands after handling the tablet, and to avoid food or beverages for 5 minutes after taking the tablet. [See Dosage and Administration (2.2).]

ALK-Abelló A/S, Bøge Allé 6-8, DK-2970 Hørsholm, Denmark

U.S. License No. 1292

Manufactured by:
Catalent Pharma Solutions Limited, Blagrove,
Swindon, Wiltshire, SN5 8RU UK

© 2022 ALK-Abelló A/S. All rights reserved.

MEDICATION GUIDE

GRASTEK® (GRAS-tek)

(Timothy Grass Pollen Allergen Extract)

Carefully read this Medication Guide before you or your child start taking GRASTEK and each time you get a refill. This Medication Guide does not take the place of talking to your doctor about your medical condition or treatment. Talk with your doctor or pharmacist if there is something you do not understand or you want to learn more about GRASTEK.

What is the Most Important Information I Should Know about GRASTEK?

GRASTEK can cause severe allergic reactions that may be life-threatening. Stop taking GRASTEK and get medical treatment right away if you or your child has any of the following symptoms after taking GRASTEK:

- Trouble breathing
- Throat tightness or swelling
- Trouble swallowing or speaking
- Dizziness or fainting
- Rapid or weak heartbeat
- Severe stomach cramps or pain, vomiting, or diarrhea
- Severe flushing or itching of the skin

For home administration of GRASTEK, your doctor will prescribe auto-injectable epinephrine, a medicine you can inject if you or your child has a severe allergic reaction after taking GRASTEK. Your doctor will train and instruct you on the proper use of auto-injectable epinephrine.

Talk to your doctor or read the epinephrine patient information if you have any questions about the use of auto-injectable epinephrine.

What is GRASTEK?

GRASTEK is a prescription medicine used for sublingual (under the tongue) immunotherapy to treat Timothy and related grass pollen allergies that can cause sneezing, runny or itchy nose, stuffy or congested nose, or itchy and watery eyes. GRASTEK may be prescribed for persons 5 through 65 years of age who are allergic to grass pollen.

GRASTEK is taken for about 12 weeks before grass pollen season and throughout grass pollen season. GRASTEK may also be taken daily for 3 years to provide a sustained effect for a fourth year in which you do not have to take GRASTEK.

GRASTEK is NOT a medication that gives immediate relief for symptoms of grass allergy.

Who Should Not Take GRASTEK?

You or your child should not take GRASTEK if:

- You or your child has severe, unstable or uncontrolled asthma
- You or your child had a severe allergic reaction in the past that included any of these symptoms:
  ○ Trouble breathing
  ○ Dizziness or fainting
  ○ Rapid or weak heartbeat
- You or your child has ever had difficulty with breathing due to swelling of the throat or upper airway after using any sublingual immunotherapy before.
- You or your child has ever been diagnosed with eosinophilic esophagitis.
- You or your child is allergic to any of the inactive ingredients contained in GRASTEK. The inactive ingredients contained in GRASTEK are: gelatin, mannitol and sodium hydroxide.

What Should I Tell My Doctor Before Taking GRASTEK?

Your doctor may decide that GRASTEK is not the best treatment if:

- You or your child has asthma, depending on how severe it is.
- You or your child suffers from lung disease such as chronic obstructive pulmonary disease (COPD)
- You or your child suffers from heart disease such as coronary artery disease, an irregular heart rhythm, or you have hypertension that is not well controlled.
- You or your daughter is pregnant, plans to become pregnant during the time you will be taking GRASTEK, or is breast-feeding.
- You or your child is unable or unwilling to administer auto-injectable epinephrine to treat a severe allergic reaction to GRASTEK.
- You or your child is taking certain medicines that enhance the likelihood of a severe reaction, or interfere with the treatment of a severe reaction. These medicines include:
  ○ beta blockers and alpha-blockers (prescribed for high blood pressure)
  ○ cardiac glycosides (prescribed for heart failure or problems with heart rhythm)
  ○ diuretics (prescribed for heart conditions and high blood pressure)
  ○ ergot alkaloids (prescribed for migraine headache)
  ○ monoamine oxidase inhibitors or tricyclic antidepressants (prescribed for depression)
  ○ thyroid hormone (prescribed for low thyroid activity).
- You or your child is receiving allergy shots or other immunotherapy under the tongue. Use of more than one of these types of medicines together may increase the likelihood of a severe allergic reaction.

You should tell your doctor if you or your child is taking or has recently taken any other medicines, including medicines obtained without a prescription and herbal supplements. Keep a list of them and show it to your doctor and pharmacist each time you get a new supply of GRASTEK. Ask your doctor or pharmacist for advice before taking GRASTEK.

Are there any reasons to stop taking GRASTEK?

Stop GRASTEK and contact your doctor if you or your child has any of the following after taking GRASTEK:

- Any type of a serious allergic reaction
- Throat tightness that worsens or swelling of the tongue or throat that causes trouble speaking, breathing or swallowing
- Asthma or any other breathing condition that gets worse
- Dizziness or fainting
- Rapid or weak heartbeat
- Severe stomach cramps or pain, vomiting, or diarrhea
- Severe flushing or itching of the skin
- Heartburn, difficulty swallowing, pain with swallowing, or chest pain that does not go away or worsens

Also, stop taking GRASTEK following: mouth surgery procedures (such as tooth removal), or if you develop any mouth infections, ulcers or cuts in the mouth or throat.

How should I take GRASTEK?

Take GRASTEK exactly as your doctor tells you.

GRASTEK is a prescription medicine that is placed under the tongue.

- Take the tablet from the blister package after carefully removing the foil with dry hands.
- Place the tablet immediately under the tongue. Allow it to remain there until completely dissolved. Do not swallow for at least 1 minute.
- Do not take GRASTEK with food or beverage. Food and beverage should not be taken for the following 5 minutes.
- Wash hands after taking the tablet.

Take the first tablet of GRASTEK in your doctor’s office. After taking the first tablet, you or your child will be watched for at least 30 minutes for symptoms of a serious allergic reaction.

If you tolerate the first dose of GRASTEK, you or your child will continue GRASTEK therapy at home by taking one tablet every day. Children should be given each tablet of GRASTEK by an adult who will watch for any symptoms of a serious allergic reaction.

Take GRASTEK as prescribed by your doctor until the end of the treatment course. If you forget to take GRASTEK, do not take a double dose. Take the next dose at your normal scheduled time the next day. If you miss more than one dose of GRASTEK, contact your healthcare provider before restarting.

What are the possible side effects of GRASTEK?

In children and adults, the most commonly reported side effects were itching of the mouth, lips, or tongue, swelling under the tongue, or throat irritation. These side effects, by themselves, were not dangerous or life-threatening.

GRASTEK can cause severe allergic reactions that may be life-threatening. Symptoms of allergic reactions to GRASTEK include:

- Trouble breathing
- Throat tightness or swelling
- Trouble swallowing or speaking
- Dizziness or fainting
- Rapid or weak heartbeat
- Severe stomach cramps or pain, vomiting, or diarrhea
- Severe flushing or itching of the skin
- High-pitched unusual breathing sound that could be a sign of trouble breathing

For additional information on the possible side effects of GRASTEK, talk with your doctor or pharmacist. You may report side effects to the U.S. Food and Drug Administration (FDA) at 1-800-FDA-1088 or www.fda.gov/medwatch.

How should I store GRASTEK?

Keep GRASTEK out of the reach of children.

Throw away any unused GRASTEK after the expiration date which is stated on the carton and blister pack after “EXP.”

Store GRASTEK in a dry place at room temperature, 15ºC to 30ºC (59ºF to 86ºF), in the original package.

General information about GRASTEK

Medicines are sometimes prescribed for purposes other than those listed in a Medication Guide. Do not use GRASTEK for a condition for which it was not prescribed. Do not give GRASTEK to other people, even if they have the same symptoms. It may harm them.

This Medication Guide summarizes the most important information about GRASTEK. If you would like more information, talk with your doctor. You can ask your doctor or pharmacist for information about GRASTEK that was written for healthcare professionals. For more information go to www.grastek.com or call toll-free at 1-855-782-9323.

This Medication Guide has been approved by the U.S. Food and Drug Administration.

Manufactured for: ALK-Abelló A/S

ALK-Abelló A/S, Bøge Allé 6-8, DK-2970 Hørsholm, Denmark

U.S. License No. 1292

Manufactured by:

Catalent Pharma Solutions Limited, Blagrove,

Swindon, Wiltshire, SN5 8RU UK

© 2019 ALK-Abelló A/S
All rights reserved.

Revised: 06/2019

PRINCIPAL DISPLAY PANEL

NDC 52709-1501-3
Timothy Grass Pollen Allergen Extract,
Grastek Tablet for Sublingual use